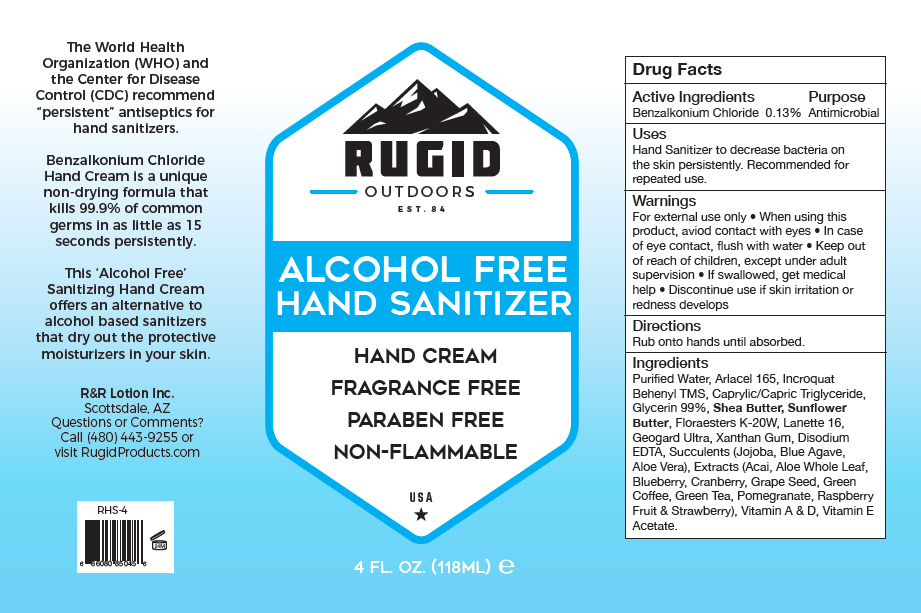 DRUG LABEL: Rugid Outdoors Hand Sanitizer Benzalkonium Chloride
NDC: 59555-910 | Form: LOTION
Manufacturer: R & R Lotion, Inc
Category: otc | Type: HUMAN OTC DRUG LABEL
Date: 20210114

ACTIVE INGREDIENTS: Benzalkonium Chloride 1.3 mg/1 mL
INACTIVE INGREDIENTS: water; Xanthan Gum; Calcium Gluconate; Sodium Benzoate; Gluconolactone; Behentrimonium Methosulfate; Cetostearyl Alcohol; Glyceryl 1-Stearate; PEG-100 Stearate; Cetyl Alcohol; MEDIUM-CHAIN TRIGLYCERIDES; Shea Butter; .ALPHA.-TOCOPHEROL; Glycerin; POTASSIUM HYDROLYZED JOJOBA ESTERS; CHOLECALCIFEROL; vitamin A

Rugid Outdoors Hand Sanitizer Benzalkonium Chloride

Drug Facts

Active Ingredients

Benzalkonium Chloride 0.13%

Purpose

Antimicrobial

Uses

Hand Sanitizer to decrease bacteria on the skin persistently. Recommended for repeated use.

Warnings

For external use only

- When using this product, aviod contact with eyes
- In case of eye contact, flush with water

- Keep out of reach of children, except under adult supervision
- If swallowed, get medical help
- Discontinue use if skin irritation or redness develops

Directions

Rub onto hands until absorbed.

Ingredients

Purified Water, Arlacel 165, Incroquat Behenyl TMS, Caprylic/Capric Triglyceride, Glycerin 99%, Shea Butter, Sunflower Butter, Floraesters K-20W, Lanette 16, Geogard Ultra, Xanthan Gum, Disodium EDTA, Succulents (Jojoba, Blue Agave, Aloe Vera), Extracts (Acai, Aloe Whole Leaf, Blueberry, Cranberry, Grape Seed, Green Coffee, Green Tea, Pomegranate, Raspberry Fruit & Strawberry), Vitamin A & D, Vitamin E Acetate.

Questions or Comments?

Call (480) 443-9255 or visit RugidProducts.com

PRINCIPAL DISPLAY PANEL - 118 ML Bottle Label

RUGID
OUTDOORS
EST. 84

ALCOHOL FREE
HAND SANITIZER

HAND CREAM

FRAGRANCE FREE

PARABEN FREE

NON-FLAMMABLE

USA

4 FL. OZ. (118ML) e